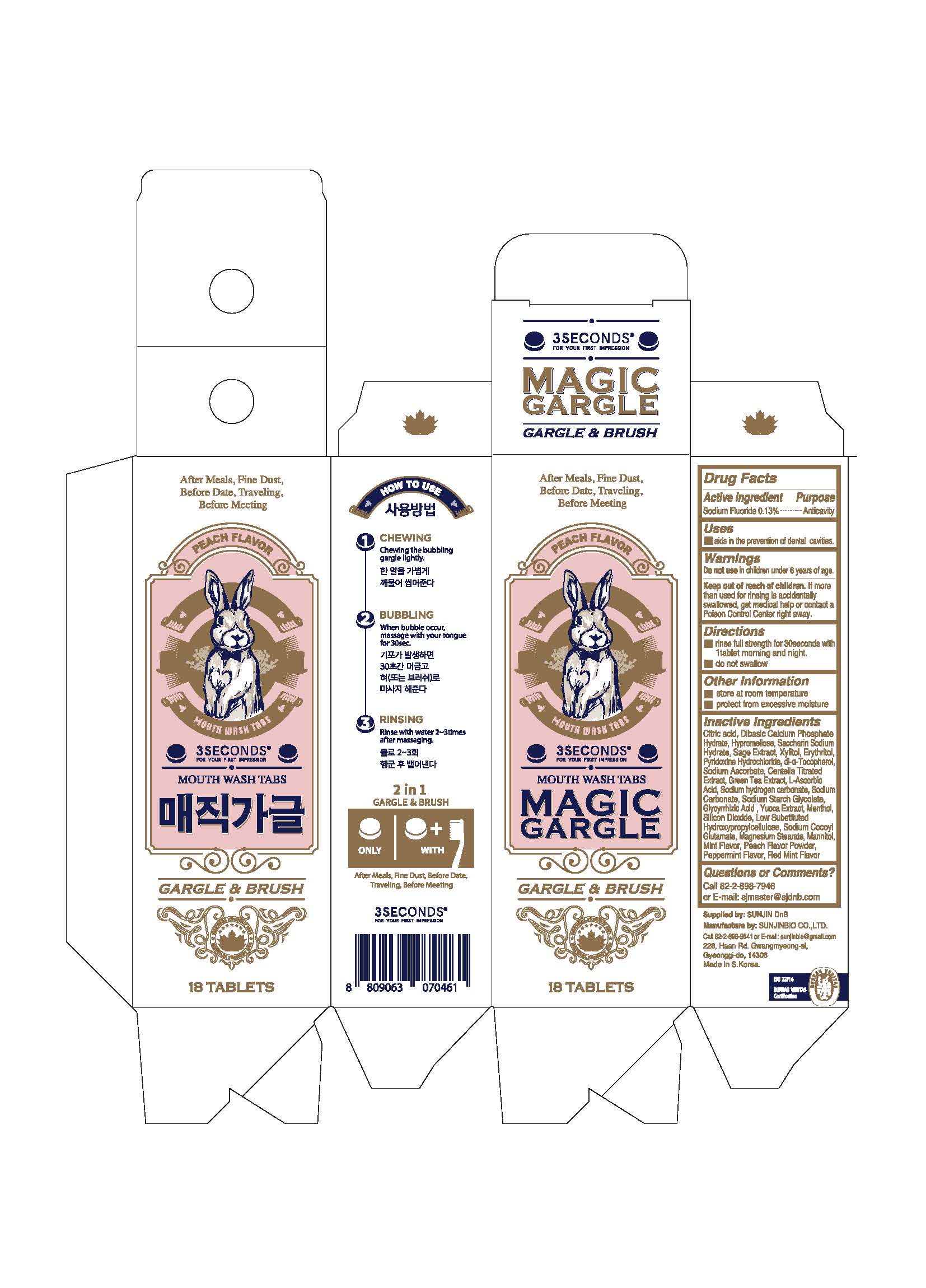 DRUG LABEL: 3SECONDS MAGIC GARGLE PEACH
NDC: 73587-0020 | Form: TABLET
Manufacturer: SUNJINBIO CO.,LTD
Category: otc | Type: HUMAN OTC DRUG LABEL
Date: 20200210

ACTIVE INGREDIENTS: SODIUM FLUORIDE 1.1 mg/1 1
INACTIVE INGREDIENTS: XYLITOL; MENTHOL

ACTIVE INGREDIENT

Sodium Flouride

PURPOSE

For dental care

Keep out of reach of children

INDICATIONS AND USAGE

1. Put one tablet in mouth.

2. Chew it.

3. Gargle for 30 sec.

4. Spit it out.

5. Rinse with water.

WARNINGS

1. The fluoride concentration of this toothpaste is 583.21 ppm.
2. Be careful not to swallow it, and rinse your mouth thoroughly after use.
3. If a child under 6 years of age swallows a large amount, consult a doctor or dentist immediately.
4. Keep out of reach of children under 6 years old.

INACTIVE INGREDIENT

MALIC ACID, HYPROMELLOSE, MALTITOL, SAGE EXTRACT, XYLITOL, GREEN TEA EXTRACT, MENTHOL, MINT FLAVOR, PEACH FLAVOR, RED MINT FLAVOR, PEPPERMINT FLAVOR, ETC.

DOSAGE AND ADMINISTRATION

For dental use only